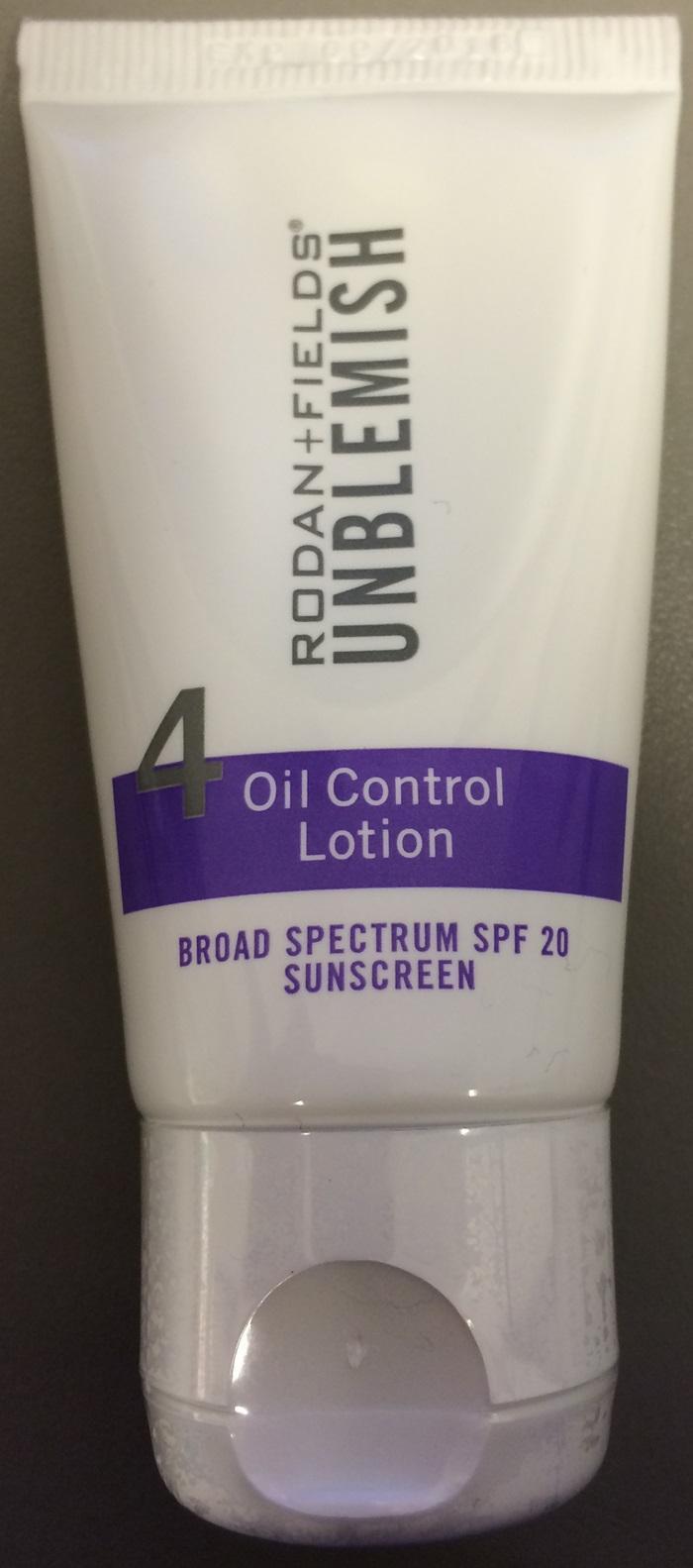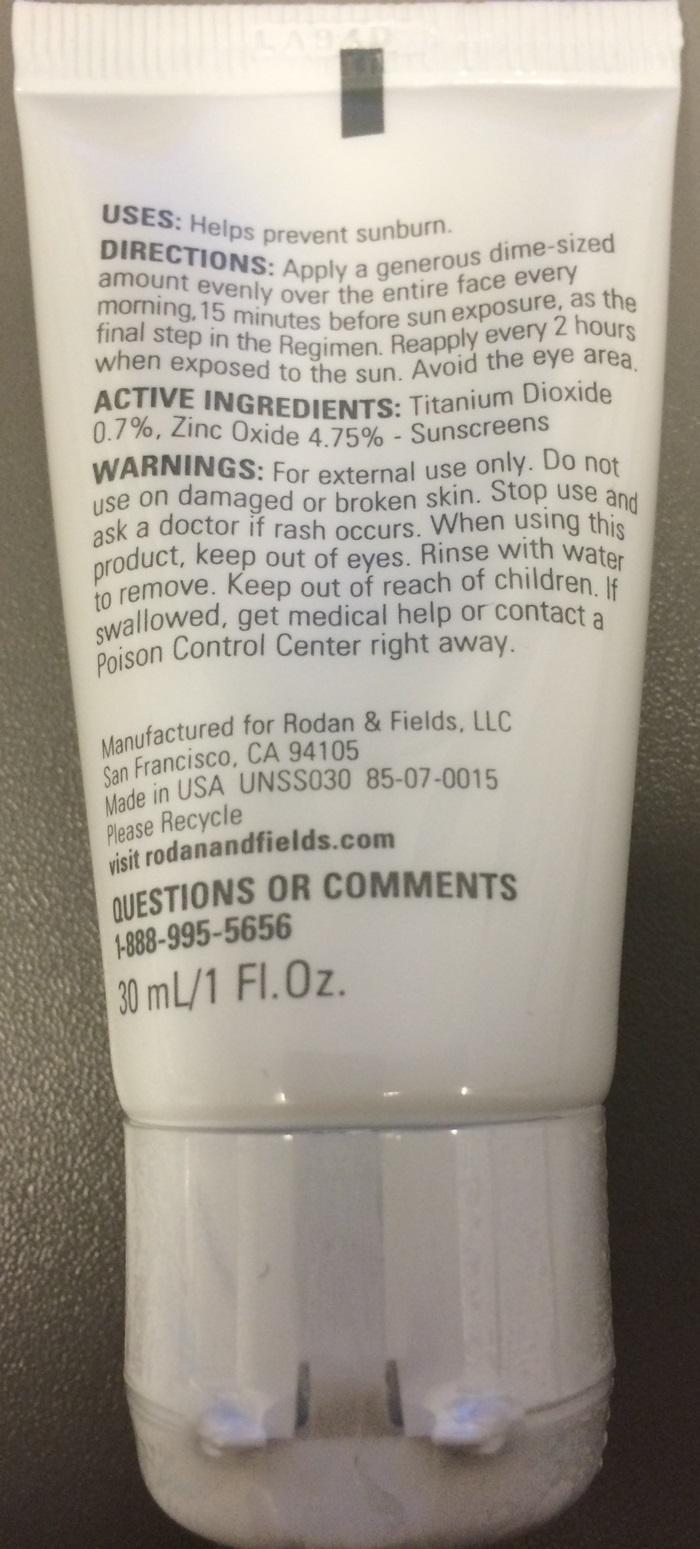 DRUG LABEL: RODAN and FIELDS UNBLEMISH
NDC: 54111-122 | Form: LOTION
Manufacturer: Bentley Laboratories, LLC
Category: otc | Type: HUMAN OTC DRUG LABEL
Date: 20241227

ACTIVE INGREDIENTS: TITANIUM DIOXIDE 0.21000 g/30 mL; ZINC OXIDE 1.42500 g/30 mL
INACTIVE INGREDIENTS: WATER; CYCLOMETHICONE 5; ISODODECANE; PENTYLENE GLYCOL; CETOSTEARYL ALCOHOL; PEG-10 DIMETHICONE (600 CST); BUTYLENE GLYCOL; POLYSORBATE 60; DIMETHICONE; HYDROXYETHYL ACRYLATE/SODIUM ACRYLOYLDIMETHYL TAURATE COPOLYMER (45000 MPA.S AT 1%); PEG-100 STEARATE; GLYCERYL MONOSTEARATE; CAPRYLYL GLYCOL; SQUALANE; CITRIC ACID MONOHYDRATE; XANTHAN GUM; 1,2-HEXANEDIOL; PEG-60 ALMOND GLYCERIDES; CETETH-10 PHOSPHATE; OLEANOLIC ACID; MASOPROCOL ; GLYCERIN; CARBOMER HOMOPOLYMER TYPE C (ALLYL PENTAERYTHRITOL CROSSLINKED); CHLORPHENESIN; DIHEXADECYL PHOSPHATE; CHOLESTEROL; HEXYL LAURATE; POLYGLYCERYL-4 ISOSTEARATE; POTASSIUM SORBATE; SODIUM BENZOATE; TOCOPHEROL; EDETATE SODIUM; TETRAHEXYLDECYL ASCORBATE; AZELAIC ACID; STEARIC ACID; EGG PHOSPHOLIPIDS; ALUMINUM OXIDE; SODIUM CHONDROITIN SULFATE (PORCINE; 5500 MW); BOERHAVIA DIFFUSA ROOT; METHYLISOTHIAZOLINONE; TROPOLONE

ACTIVE INGREDIENTS:

Titanium Dioxide 0.7%
Zinc Oxide 4.75%

PURPOSE:

Sunscreens

Keep out of reach of children. If swallowed, get medical help or contact a Poison Control Center right away.

USES:

Helps prevent sunburn.

WARNINGS:

For external use only. Do not use on damaged or broken skin. Stop use and ask a doctor if rash occurs. When using this product, keep out of eyes. Rinse with warm water to remove.

DIRECTIONS:

Apply a generous dime-sized amount evenly over the entire face every morning, 15 minutes before sun exposure, as the final step in the Regimen. Reapply every 2 hours when exposed to the sun. Avoid the eye area.

INACTIVE INGREDIENTS:

Water, Cyclopentasiloxane, Isododecane, Pentylene Glycol, Cetearyl Alcohol, Polysilicone-11, PEG-10 Dimethicone, Butylene Glycol, Polysorbate 60, Dimethicone, Hydroxyethyl Acrylate/Sodium Acryloyldimethyl Taurate Copolymer, PEG-100 Stearate, Glyceryl Stearate, Caprylyl Glycol, Squalane, Citric Acid, Xanthan Gum, 1,2-Hexanediol, PEG-60 Almond Glycerides, Ceteth-10 Phosphate, Oleanolic Acid, Nordihydroguaiaretic Acid, Glycerin, Carbomer, Chlorphenesin, Dimethiconol, Dicetyl Phosphate, Cholesterol, Hexyl Laurate, Fragrance, Polyglyceryl-4 Isostearate, Potassium Sorbate, Sodium Benzoate, Tocopherol, Disodium EDTA, Tetrahexyldecyl Ascorbate, Azelaic Acid, Stearic Acid, Lecithin, Alumina, Sodium Chondroitin Sulfate, Atelocollagen, Boerhavia Diffusa Root Extract, Methylisothiazolinone, Tropolone

RODAN and FIELDS UNBLEMISHED Label

RODAN and FIELDS UNBLEMISHED

4 Oil Control Lotion

BROAD SPECTRUM SPF 20 SUNSCREEN

Manufactured for Rodan and Fields, LLC
San Francisco, CA 94105
Made in USA UNSS030 85-07-0015
Please recycle
visit rodanandfields.com

QUESTIONS OR COMMENTS
1-888-995-5656

30mL/1 Fl. Oz.